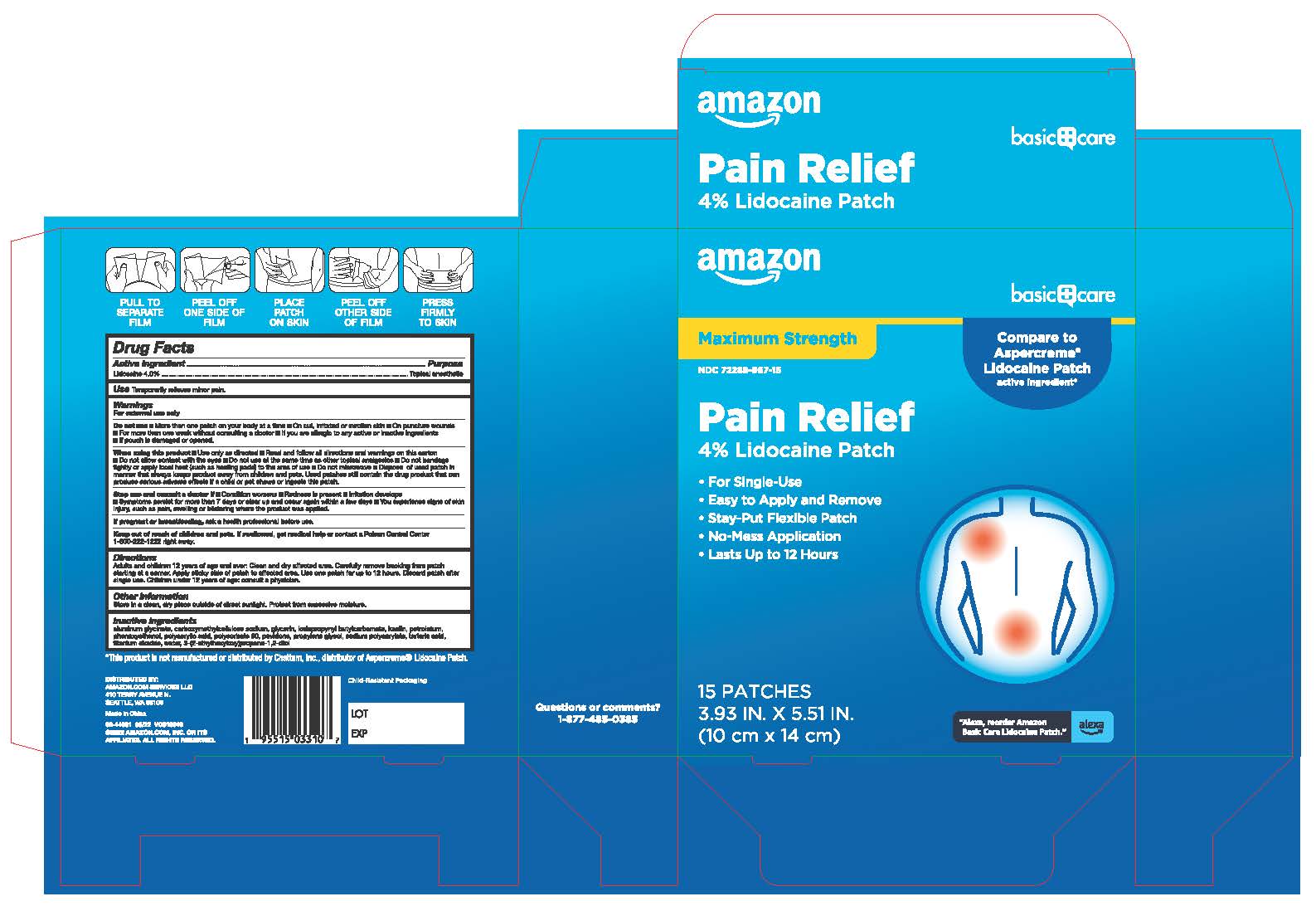 DRUG LABEL: Amazon Basics Pain Relief Patch with 4% Lidocaine
NDC: 72288-967 | Form: PATCH
Manufacturer: Amazon.com Services LLC
Category: otc | Type: HUMAN OTC DRUG LABEL
Date: 20251228

ACTIVE INGREDIENTS: LIDOCAINE 4 g/100 g
INACTIVE INGREDIENTS: GLYCERIN; SODIUM POLYACRYLATE (8000 MW); DIHYDROXYALUMINUM AMINOACETATE; KAOLIN; POLYSORBATE 80; PROPYLENE GLYCOL; WATER; POLYACRYLIC ACID (8000 MW); CARBOXYMETHYLCELLULOSE SODIUM; TITANIUM DIOXIDE; TARTARIC ACID; ETHYLHEXYLGLYCERIN; PHENOXYETHANOL; IODOPROPYNYL BUTYLCARBAMATE; POVIDONE; PETROLATUM

Amazon Basics Pain Relief Patch with 4% Lidocaine

Active Ingredient

Lidocaine 4.0%

Purpose

Topical anesthetic

Use

Temporarily relieves minor pain.

Warnings

For external use only

Do not Use

■ More than one patch on your body at a time■ On cut. irritated or swollen skin■ On puncture wounds

For more than one week without consulting a doctor■ If you are allergic to any active or inactive ingredients

If pouch is damaged or opened

When using this product

■ Use only as directed ■ Read and follow all directions and warnings on this carton

■ Do not allow contact with the eyes■ Do not use at the same time as other topical analgesics■ Do not bandage lightly or apply local heat (such as heating pads) to the area of use ■ Do not microwave■ Dispose of used patch in manner that always keeps product away from children and pets. Used patches still contain the drug product that can produce serious adverse effects if a child or pet chews or ingests this patch.

Stop use and consult a doctor

■ Condition worsens ■ Redness is present ■ Irritation develops

■ Symptoms persist for more than 7 days or clear up and occur again within a few days ■ You experience signs of skin

injury. such as pain, swelling or blistering where the product was applied.

If pregnant or breastfeeding

ask a health professional before use

Keep out of reach of children and pets

If swallowed, get medical help or contact a Poison Control Center 1-800-222-1222 right away.

Directions

Adults and children 12 years of age and over: Clean and dry affected area. Carefully remove backing from patch starting at a corner. Apply sticky side of patch to affected area. Use one patch for up to 12 hours. Discard patch after single use. Children under 12 years of age: consult a physician.

Other Information

Store in a clean, dry place outside of direct sunlight. Protect from excessive moisture.

Inactive Ingredients

aluminum glycinate, carboxymethylcellulose sodium, glycerin, iodopropynyl butylcarbamate, kaolin, petrolatum, phenoxyethanol, polyacrylic acid, polysorbate 80, povidone, propylene glycol, sodium polyacrylate, tartaric acid, titanium dioxide, water, 3-(2-ethylhexyloxy)propane-1,2-diol